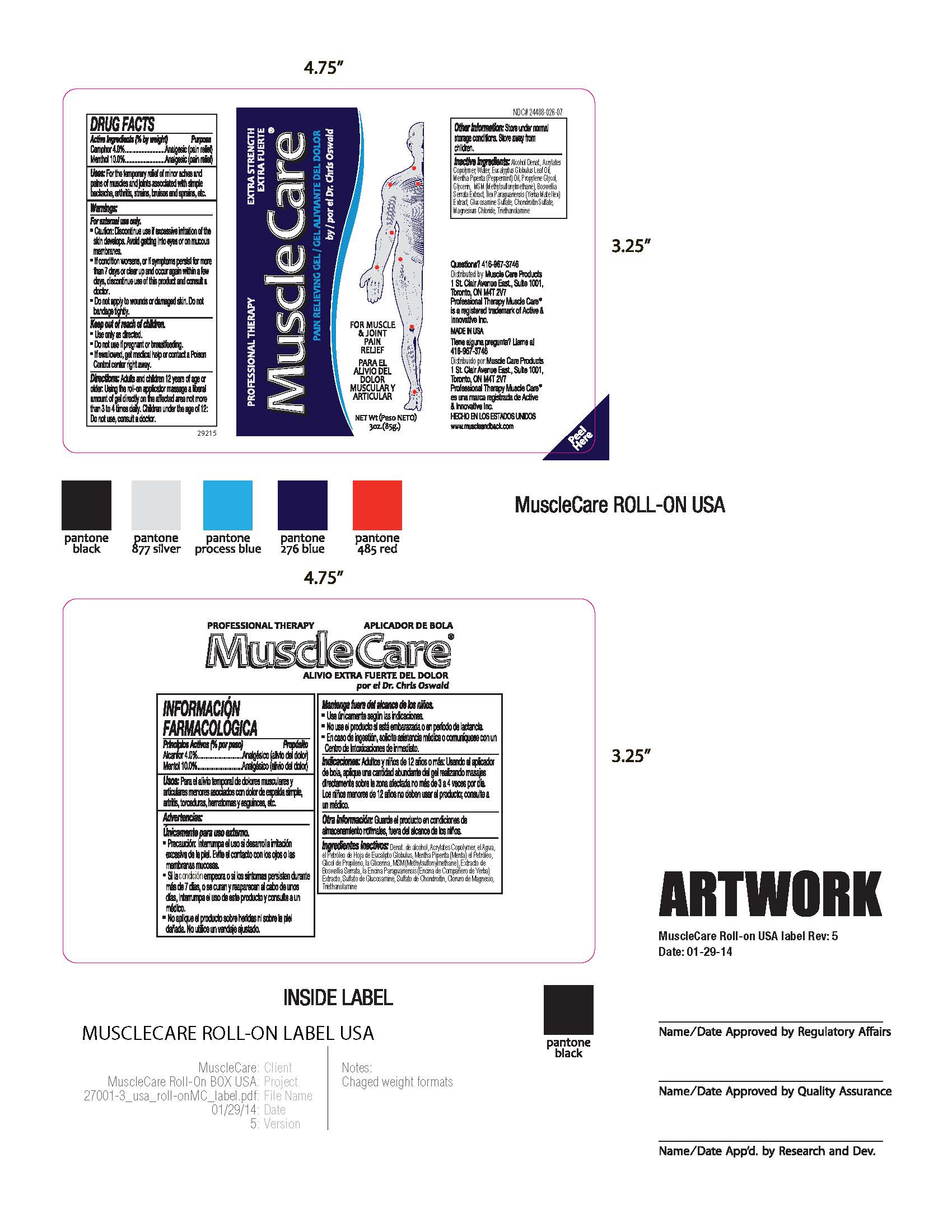 DRUG LABEL: Professional Therapy MuscleCare pain relieving gel
NDC: 70039-283 | Form: GEL
Manufacturer: Active and Innovative Inc.
Category: otc | Type: HUMAN OTC DRUG LABEL
Date: 20160810

ACTIVE INGREDIENTS: CAMPHOR (SYNTHETIC) 40 mg/1 g; MENTHOL 100 mg/1 g
INACTIVE INGREDIENTS: PROPYLENE GLYCOL; ETHYL ACRYLATE/METHACRYLIC ACID/STEARETH-20 METHACRYLATE COPOLYMER; WATER; EUCALYPTUS OIL; PEPPERMINT OIL; GLYCERIN; DIMETHYL SULFONE; CHONDROITIN SULFATE (CHICKEN); MAGNESIUM CHLORIDE; INDIAN FRANKINCENSE; ILEX PARAGUARIENSIS LEAF; GLUCOSAMINE SULFATE; ALCOHOL; TROLAMINE

Professional Therapy MuscleCare pain relieving gel, 3 oz roll-on

Active Ingredients (% by weight) Purpose

Camphor 4.0%................................Analgesic (pain relief)

Menthol 10.0%.................................Analgesic (pain relief)

Uses:

For temporary relief of minor aches and pains of muscles and joints associated with simple backache, arthritis, strains, bruises and sprains, etc.

Warnings:

For external use only.

- Caution: Discontinue use if excessive irritation of the skin develops. Avoid getting into eyes or on mucous membranes

- If condition worsens, or if symptoms persist for more than 7 days or clear up and occur again within a few days, discontinue use of this product and consult a doctor.

- Do not apply to wounds or damaged skin. Do not bandage tightly.

Keep out of reach of children.

- Use only as directed.

- Do not use if pregnant or breastfeeding.

- If swallowed, get medical help or contact a Poison Control center right away.

Directions:

Adults and children 12 years of age or older: Using the roll-on applicator massage a liberal amount of gel directly on the affected area not more than 3 to 4 times daily. Children under the age of 12: Do not use, consult a doctor.

Other Information:

Store under normal storage conditions. Store away from children.

Inactive Ingredients:

Alcohol Denat., Acrylates Copolymer, Water, Eucalyptus Globulus Leaf Oil, Mentha Piperita (Peppermint Oil), Propylene Glycol, Glycerin, MSM (Methylsulfonylmethane), Boswellia Serrata Extract, Ilex Paraguensis (Yerba Mate Ilex) Extract, Glucosamine Sulfate, Chondroitin Sulfate, Magnesium Chloride, Triethanolamine.

PURPOSE

FOR MUSCLE & JOINT PAIN RELIEF

PACKAGE LABEL

Extra Strength Pain Relieving Gel

by Dr. Chris Oswald

Net Wt

3oz. (85g)